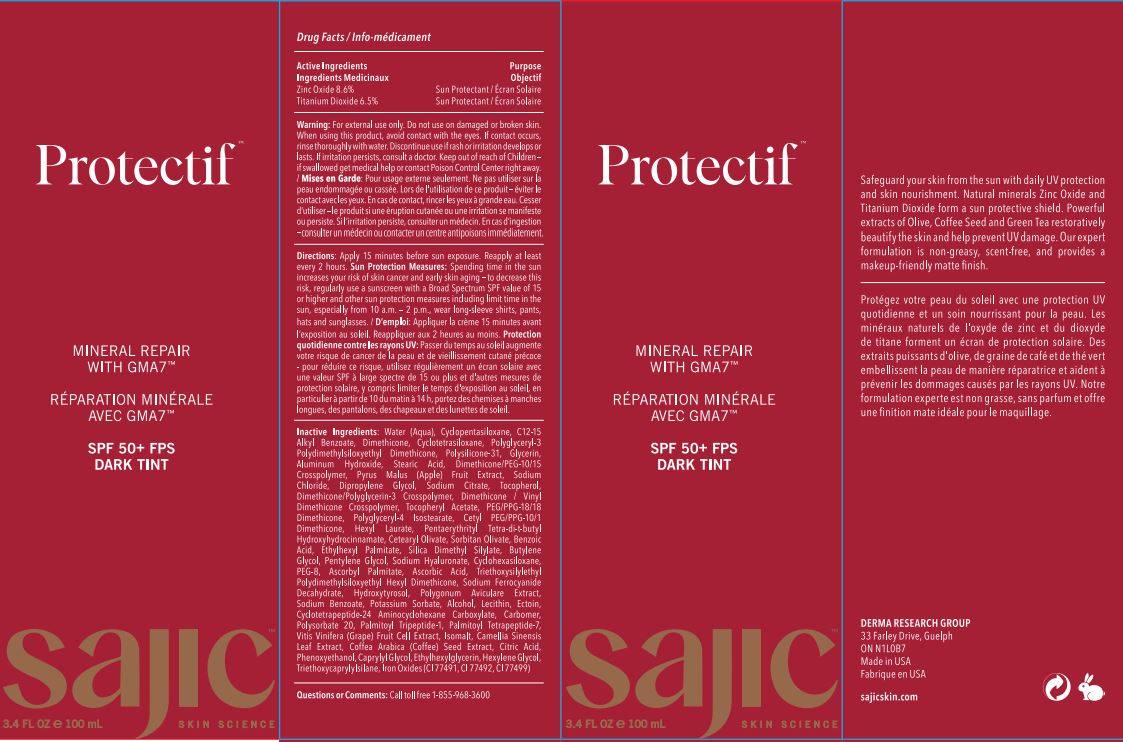 DRUG LABEL: Protectif deep tint
NDC: 82038-002 | Form: CREAM
Manufacturer: Derma Research Group Inc.
Category: otc | Type: HUMAN OTC DRUG LABEL
Date: 20220625

ACTIVE INGREDIENTS: TITANIUM DIOXIDE 6.5 g/100 g; ZINC OXIDE 8.6 g/100 g
INACTIVE INGREDIENTS: DIPROPYLENE GLYCOL; APPLE; ETHYLHEXYLGLYCERIN; CYCLOTETRAPEPTIDE-24 AMINOCYCLOHEXANE CARBOXYLATE; LECITHIN, SOYBEAN; FERROSOFERRIC OXIDE; VINYL DIMETHICONE/METHICONE SILSESQUIOXANE CROSSPOLYMER; .ALPHA.-TOCOPHEROL ACETATE; PENTAERYTHRITOL TETRAKIS(3-(3,5-DI-TERT-BUTYL-4-HYDROXYPHENYL)PROPIONATE); SILICA DIMETHYL SILYLATE; CETYL PEG/PPG-10/1 DIMETHICONE (HLB 4); POLYETHYLENE GLYCOL 400; ALCOHOL; POLYSORBATE 20; SODIUM CHLORIDE; SORBITAN OLIVATE; ISOMALT; GREEN TEA LEAF; ARABICA COFFEE BEAN; TRIETHOXYCAPRYLYLSILANE; FERRIC OXIDE RED; FERRIC OXIDE YELLOW; DIMETHICONE; CYCLOMETHICONE 4; HYDROXYTYROSOL; BENZOIC ACID; HYALURONATE SODIUM; CYCLOMETHICONE 6; ASCORBYL PALMITATE; SODIUM FERROCYANIDE DECAHYDRATE; POTASSIUM SORBATE; CETEARYL OLIVATE; CITRIC ACID MONOHYDRATE; PHENOXYETHANOL; PEG/PPG-18/18 DIMETHICONE; POLYGLYCERYL-4 ISOSTEARATE; HEXYL LAURATE; ECTOINE; ALKYL (C12-15) BENZOATE; GLYCERIN; ALUMINUM HYDROXIDE; SODIUM CITRATE; DIMETHICONE/POLYGLYCERIN-3 CROSSPOLYMER; ETHYLHEXYL PALMITATE; PENTYLENE GLYCOL; HEXYLENE GLYCOL; DIMETHICONE/PEG-10/15 CROSSPOLYMER; ASCORBIC ACID; POLYGONUM AVICULARE TOP; SODIUM BENZOATE; CARBOMER HOMOPOLYMER, UNSPECIFIED TYPE; VITIS VINIFERA STEM; CAPRYLYL GLYCOL; DIMETHICONE/VINYL DIMETHICONE CROSSPOLYMER (SOFT PARTICLE); WATER; POLYGLYCERYL-3 POLYDIMETHYLSILOXYETHYL DIMETHICONE (4000 MPA.S); TOCOPHEROL; CYCLOMETHICONE 5; STEARIC ACID; BUTYLENE GLYCOL; TRIETHOXYSILYLETHYL POLYDIMETHYLSILOXYETHYL HEXYL DIMETHICONE; PALMITOYL TRIPEPTIDE-1; PALMITOYL TETRAPEPTIDE-7

Drug Facts

Active Ingredients

Zinc Oxide 8.6 %

Titanium Dioxide 6.5 %

Purpose

Sun Protectant

Uses

Helps Prevent sunburn

Warning

For external use only.

Do not use on damaged or broken skin.

When using this product, avoid contect with eyes.If contect occurs, rinse throughly with water.

stop use

Discontinue use if rash or irritation develops or lasts. If irritation persists,consultant a doctor

Keep out of reach of children

If swallowed get medical help or contect poison control center right away.

DOSAGE AND ADMINISTRATION

Directions: Apply 15 minutes before sun exposure

Reapply at least every 2 hours Sun Protection Measures Spending time in the sun increases your risk of skin cancer and early skin aging to decrease this risk regularly use a sunscreen with a Broad Spectrum SPF value of 15 or higher and other sun protection measures including limit time in the sun especially from 10 am to 2 pm wear long sleeve shirts pants hats and sunglasses

OTHER SAFETY INFORMATION

NA

Inactive Ingredients:

Water (Aqua), Cyclopentasiloxane,C12-15 Alkyl Benzoate,Dimethicone,Cyclotetrasiloxane,Polyglyceryl-3 Polydimethylsiloxyethyl Dimethicone, Polysilicone-31,Glycerin,Aluminum Hydroxide,Stearic Acid,Dimethicone/PEG-10/15 Crosspolymer,Pyrus Malus (Apple) Fruit Extract,Sodium Chloride,Dipropylene Glycol,Sodium Citrate,Tocopherol,Dimethicone/Polyglycerin-3 Crosspolymer,

Dimethicone / Vinyl Dimethicone Crosspolymer,Tocopheryl Acetate,PEG/PPG-18/18 Dimethicone,Polyglyceryl-4 Isostearate,

Cetyl PEG/PPG-10/1 Dimethicone,Hexyl Laurate,Pentaerythrityl Tetra-di-t-butyl Hydroxyhydrocinna mate, Cetearyl Olivate,

Sorbitan Olivate, Benzoic Acid,Ethylhexyl Palmitate,Silica Dimethyl Silylate, Butylene Glycol,Pentylene Glycol,

Sodium Hyaluronate, Cyclohexasiloxane,PEG-8, Ascorbyl Palmitate, Ascorbic Acid,Triethoxysilylethyl Polydimethylsiloxyethyl Hexyl Dimethicone,Sodium Ferrocyanide Decahydrate,Hydroxytyrosol, Polygonum Aviculare Extract,Sodium Benzoate,

Potassium Sorbate,Alcohol,Lecithin,Ectoin,Cyclotetrapeptide-24 Aminocyclohexane Carboxylate,Carbomer,

Polysorbate 20,Palmitoyl Tripeptide-1, Palmitoyl Tetrapeptide-7,Vitis Vinifera (Grape) Fruit Cell Extract,

Isomalt,Camellia Sinensis Leaf Extract,Coffea Arabica (Coffee) Seed Extract, Citric Acid,Phenoxyethanol,Caprylyl Glycol,

Ethylhexylglycerin,Hexylene Glycol,Triethoxycaprylylsilane, Iron Oxides (CI 77491, CI 77492, CI 77499)